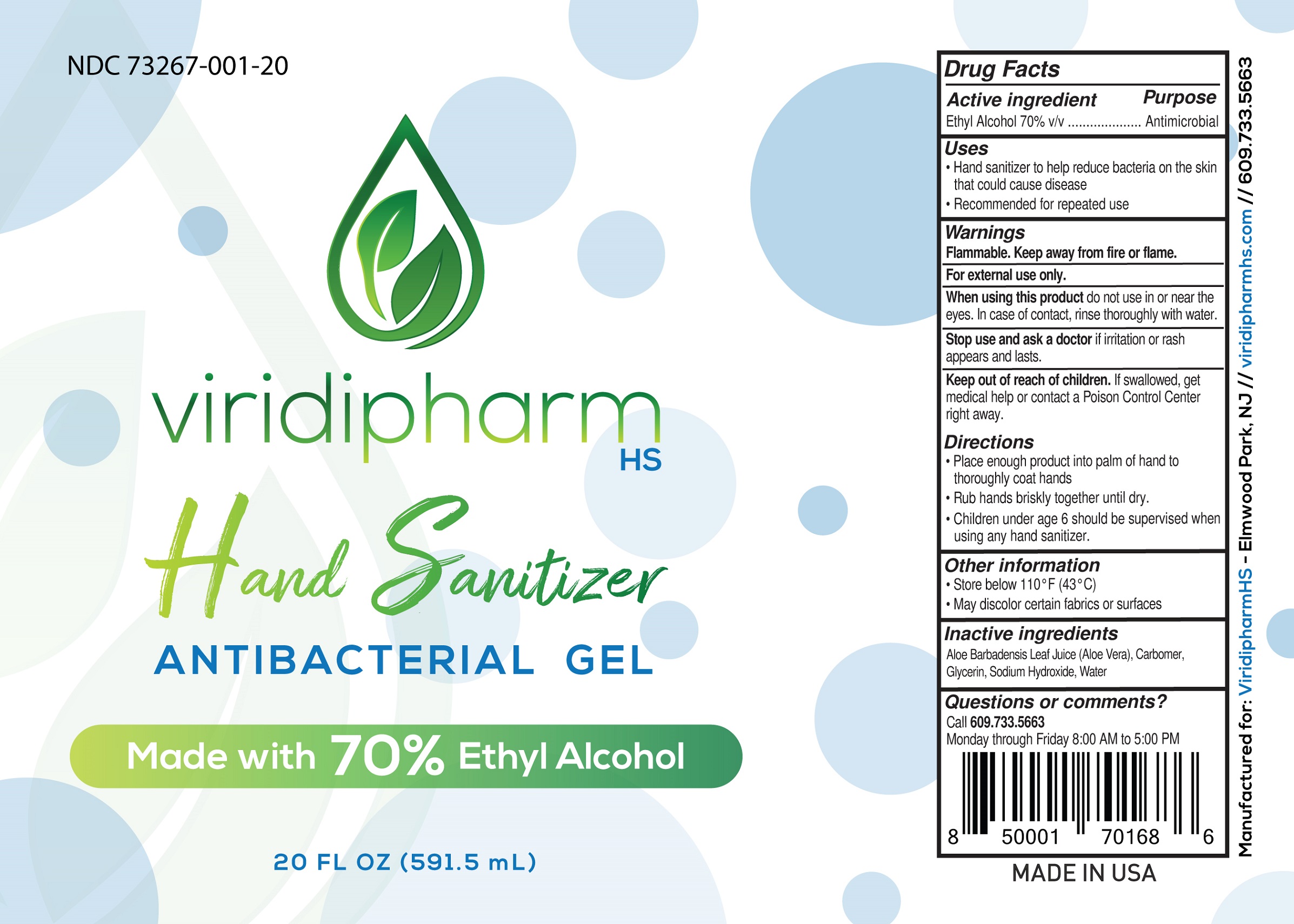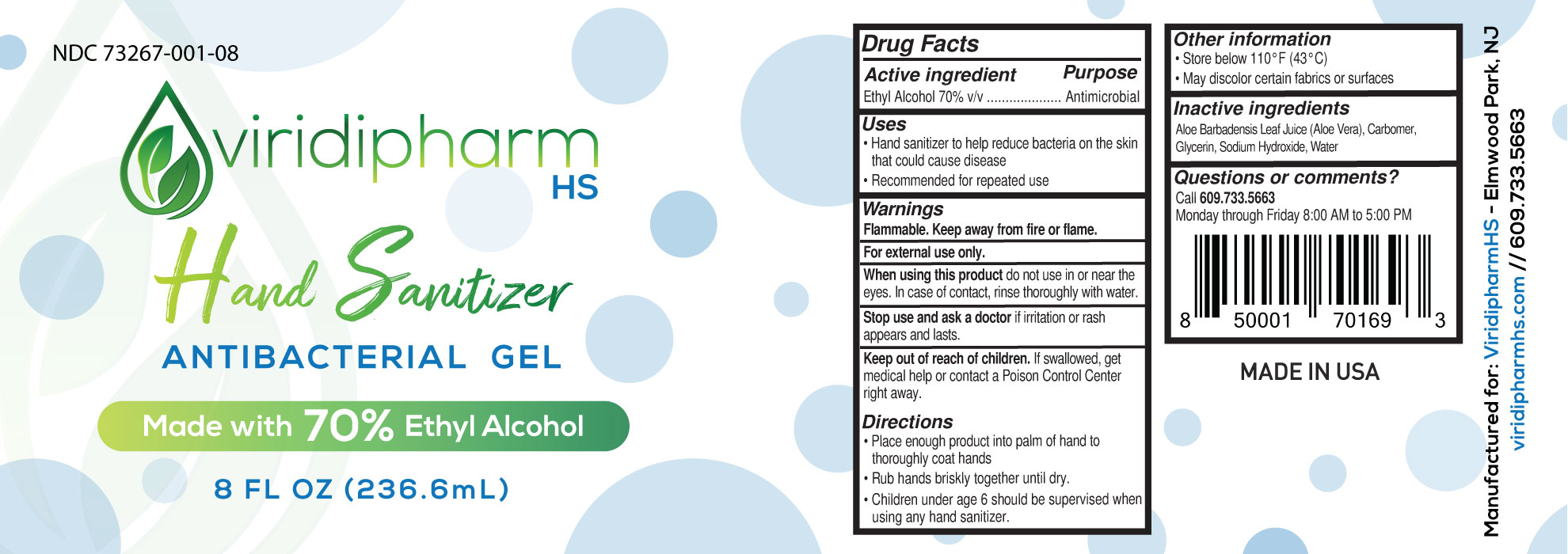 DRUG LABEL: Viridipharm Hand Sanitizer Antibacterial
NDC: 73267-001 | Form: GEL
Manufacturer: Viridipharm, LLC
Category: otc | Type: HUMAN OTC DRUG LABEL
Date: 20200513

ACTIVE INGREDIENTS: ALCOHOL 70 mL/100 mL
INACTIVE INGREDIENTS: GLYCERIN; ALOE VERA LEAF; WATER; CARBOMER HOMOPOLYMER, UNSPECIFIED TYPE; SODIUM HYDROXIDE

Viridipharm Hand Sanitizer Antibacterial Gel

Active Ingredient(s)

Alcohol 70% v/v

Purpose

Antimicrobial

Use

- Hand sanitizer to help reduce bacteria on the skin that could cause disease
- Recommended for repeated use

Warnings

Flammable. Keep away from fire or flame.

For external use only.

When using this product do not use in or near the eyes. In case of contact, rinse thoroughly with water.

Stop use and ask a doctor if irritation or rash appears and lasts.

Keep out of reach of children. If swallowed, get medical help or contact a Poison Control Center right away.

Directions

- Place enough product in your palm to thoroughly cover your hands.
- Rub hands together briskly until dry.
- Children under 6 years of age should be supervised when using this product.

Other information

- Store below 110 F (43 C)
- May discolor certain fabrics or surfaces

Inactive ingredients

Aloe Barbadensis Leaf Juice (Aloe Vera), Carbomer, Glycerin, Sodium Hydroxide, Water

Questions or comments?

Call 609.733.5663

Monday through Friday 8:00 AM to 5:00 PM